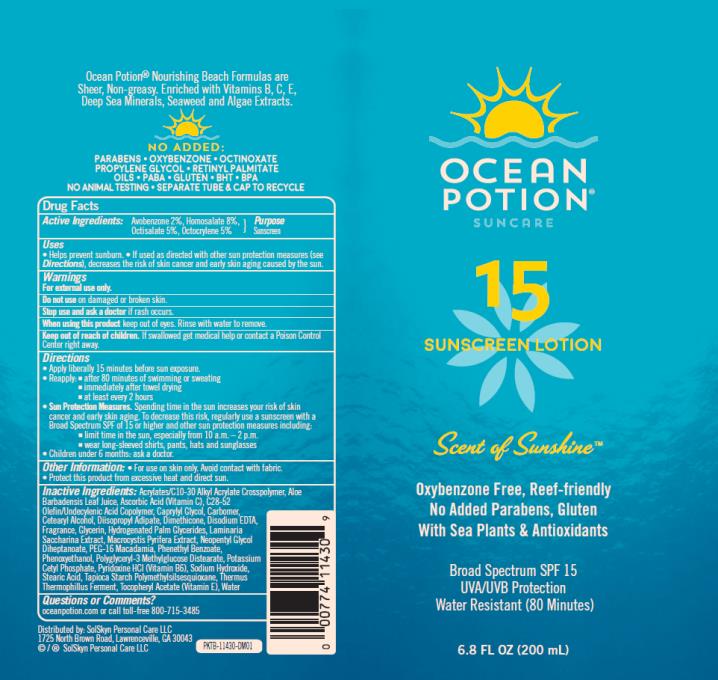 DRUG LABEL: Ocean Potion SPF15 Sunscreen
NDC: 70281-506 | Form: LOTION
Manufacturer: SolSkyn Personal Care LLC
Category: otc | Type: HUMAN OTC DRUG LABEL
Date: 20180221

ACTIVE INGREDIENTS: AVOBENZONE 2 mg/100 mg; HOMOSALATE 8 mg/100 mg; OCTISALATE 5 mg/100 mg; OCTOCRYLENE 5 mg/100 mg
INACTIVE INGREDIENTS: CARBOMER INTERPOLYMER TYPE A (55000 CPS); ALOE VERA LEAF; ASCORBIC ACID; CAPRYLYL GLYCOL; CARBOXYPOLYMETHYLENE; CETOSTEARYL ALCOHOL; DIISOPROPYL ADIPATE; DIMETHICONE; EDETATE DISODIUM ANHYDROUS; GLYCERIN; HYDROGENATED PALM GLYCERIDES; SACCHARINA LATISSIMA; MACROCYSTIS PYRIFERA; NEOPENTYL GLYCOL DIHEPTANOATE; PEG-16 MACADAMIA GLYCERIDES; PHENETHYL BENZOATE; PHENOXYETHANOL; POTASSIUM CETYL PHOSPHATE; PYRIDOXINE HYDROCHLORIDE; SODIUM HYDROXIDE; STEARIC ACID; THERMUS THERMOPHILUS LYSATE; .ALPHA.-TOCOPHEROL ACETATE; WATER

OP SPF 15 200ml

OP SPF 15 Lotion

Active Ingredients

Avobenzone 2%, Homosalate 8%, Octisalate 5%, Octocrylene 5%

Purpose

Sunscreen

Uses

- helps prevent sunburn
- if used as directed with other sun protection measures (see Directions), decreases the risk of skin cancer and early skin aging caused by the sun

Warnings

- For external use only
- Flammable: keep away from fire or flame.

When using this product keep out of eyes.

Rinse with water to remove.

Keep out of reach of children.

If product is swallowed, get medical help or contact a Poison Control Center right away.

Directions

- apply liberally 15 minutes before sun exposure
- re-apply:
  • after 80 minutes of swimming or sweating
  • immediately after towel drying
  • at least every 2 hours

Sun Protection Measures. Spending time in the sun increases your risk of skin cancer and early skin aging. To decrease this risk, regularly use a sunscreen with broad spectrum SPF of 15 or higher and other sun protection measures including:

- limit time in the sun, especially from 10 a.m.-2 p.m.
- wear long-sleeved shirts, pants, hats and sunglasses
- children under 6 months: ask a doctor

Other information

- protect this product from excessive heat and direct sun
- For use on skin only. Avoid contact with fabric.

Inactive Ingredients

Acrylates/C10-30 Alkyl Acrylate Crosspolymer, Aloe Barbadensis Leaf Juice, Ascorbic Acid (Vitamin C), C28-52 Olefin/Undecylenic Acid Copolymer, Caprylyl Glycol, Carbomer, Cetearyl Alcohol, Diisopropyl Adipate, Dimethicone, Disodium EDTA, Fragrance, Glycerin, Hydrogenated Palm Glycerides, Laminaria Saccharina Extract, Macrocystis Pyrifera Extract, Neopentyl Glycol Diheptanoate, PEG-16 Macadamia, Phenethyl Benzoate, Phenoxyethanol, Polyglyceryl-3 Methylglucose Distearate, Potassium Cetyl Phosphate, Pyridoxine HCl (Vitamin B6), Sodium Hydroxide, Stearic Acid, Tapioca Starch Polymethylsilsesquioxane, Thermus Thermophillus Ferment, Tocopheryl Acetate (Vitamin E), Water

Questions or comments?

www.oceanpotion.com call toll-free 1-800-715-3485

MAY STAIN SOME FABRICS, PLASTICS AND WOOD SURFACES.

PRINCIPAL DISPLAY PANEL

OCEAN
POTION
SUNCARE
15
SUNSCREEN LOTION
Scent of sunshine
6.8 FL OZ (200 mL)